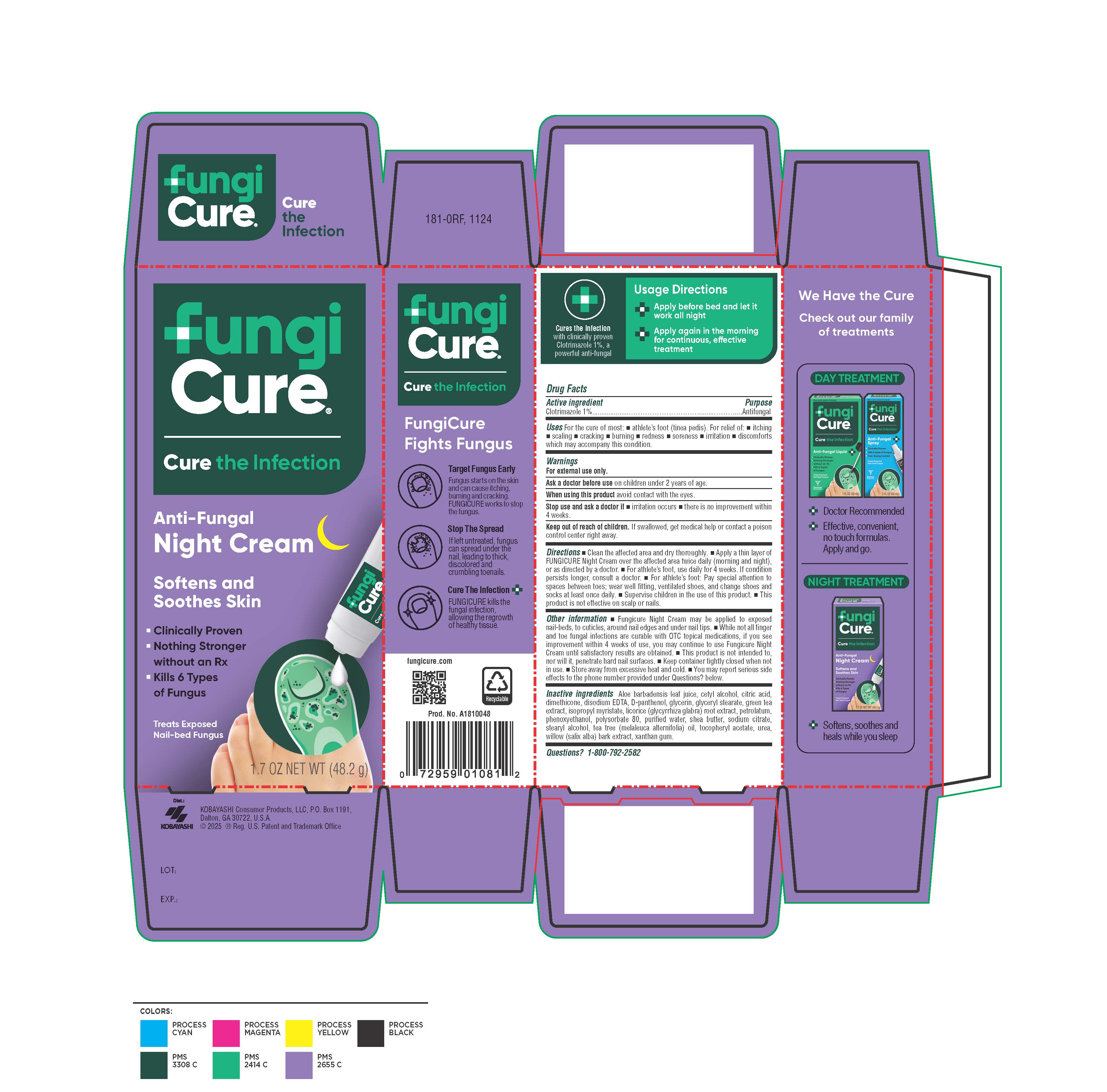 DRUG LABEL: Fungicure Night Cream
NDC: 52389-681 | Form: CREAM
Manufacturer: Kobayashi Healthcare International, Inc.
Category: otc | Type: HUMAN OTC DRUG LABEL
Date: 20251204

ACTIVE INGREDIENTS: CLOTRIMAZOLE 10 mg/1 g
INACTIVE INGREDIENTS: GLYCYRRHIZA GLABRA (LICORICE) ROOT; GREEN TEA LEAF; STEARYL ALCOHOL; PHENOXYETHANOL; ALOE BARBADENSIS LEAF JUICE; WHITE PETROLATUM; TEA TREE OIL; XANTHAN GUM; WATER; CITRIC ACID; .ALPHA.-TOCOPHEROL ACETATE; UREA; POLYSORBATE 80; GLYCERIN; GLYCERYL STEARATE SE; CETYL ALCOHOL; WILLOW BARK; SHEA BUTTER; DISODIUM HEDTA; PANTHENOL; ISOPROPYL MYRISTATE; DIMETHICONE 350; TRISODIUM CITRATE DIHYDRATE

Fungicure Night Cream

Active ingredient

Clotrimazole 1%

Purpose

Antifungal

Uses

For the cure of most

- athlete's foot (tinea pedis)

For relief og:

- itching
- scaling
- cracking
- burning
- redness
- soreness
- irritation
- discomforts which may accompany this condition.

Warnings

For external use only.

Ask a doctor before use

on children under 2 years of age.

When using this product

avoid contact with the eyes.

Stop use and ask a doctor if

- irritation occurs
- there is no improvement within 4 weeks.

Keep out of reach of children.

If swallowed, get medical help or contact a poison control center right away.

Directions

- Clean the affected area and dry thoroughly.
- Apply a thin layer of FUNGICURE Night Cream over the affected area twice daily (morning and night), or as directed by a doctor.
- For athlete's foot, use daily for 4 weeks. If condition persists longer, consult a doctor.
- For athlete's foot: Pay special attention to spaces between toes; wear well fitting, ventilated shoes, and change shoes and socks at least once daily.
- Supervise children in the use of this product.
- This product is not effective on scalp or nails.

Other information

- Fungicure Night Cream may be applied to exposed nail-beds, to cuticles, around nail edges and under nail tips.
- While not all finger and toe fungal infections are curable with OTC topical medications, if you see improvement within 4 weeks of use, you may continue to use Fungicure Night Cream until satisfactory results are obtained.
- This product is not intended to, nor will it, penetrate hard nail surfaces.
- Keep container tightly closed when not in use.
- Store away from excessive heat and cold.
- You may report serious side effects to the phone number provided under Questions? below.

Inactive ingredients

Aloe barbadensis leaf juice, cetyl alcohol, citric acid, dimethicone, disodium EDTA, D-panthenol, glycerin, glyceryl stearate, green tea extract, isopropyl myristate, licorice (glycyrrhiza glabra) root extract, petrolatum, phenoxyethanol, polysorbate 80, purified water, shea butter, sodium citrate, stearyl alcohol, tea tree (melaleuca alternifolia) oil, tocopheryl acetate, urea, willow (salix alba) bark extract, xanthan gum.

Questions?

1-800-792-2582